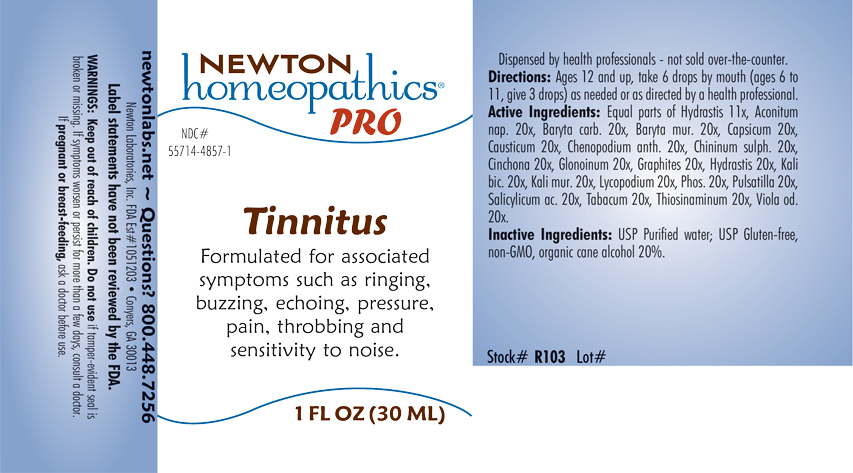 DRUG LABEL: Tinnitus
NDC: 55714-4857 | Form: LIQUID
Manufacturer: Newton Laboratories, Inc.
Category: homeopathic | Type: HUMAN OTC DRUG LABEL
Date: 20240131

ACTIVE INGREDIENTS: ACONITUM NAPELLUS 20 [hp_X]/1 mL; BARIUM CARBONATE 20 [hp_X]/1 mL; BARIUM CHLORIDE DIHYDRATE 20 [hp_X]/1 mL; CAPSICUM 20 [hp_X]/1 mL; CAUSTICUM 20 [hp_X]/1 mL; DYSPHANIA AMBROSIOIDES 20 [hp_X]/1 mL; QUININE SULFATE 20 [hp_X]/1 mL; CINCHONA OFFICINALIS BARK 20 [hp_X]/1 mL; NITROGLYCERIN 20 [hp_X]/1 mL; GRAPHITE 20 [hp_X]/1 mL; GOLDENSEAL 20 [hp_X]/1 mL; POTASSIUM DICHROMATE 20 [hp_X]/1 mL; POTASSIUM CHLORIDE 20 [hp_X]/1 mL; LYCOPODIUM CLAVATUM SPORE 20 [hp_X]/1 mL; ANEMONE PULSATILLA 20 [hp_X]/1 mL; SALICYLIC ACID 20 [hp_X]/1 mL; TOBACCO LEAF 20 [hp_X]/1 mL; ALLYLTHIOUREA 20 [hp_X]/1 mL; VIOLA ODORATA 20 [hp_X]/1 mL; PHOSPHORUS 20 [hp_X]/1 mL
INACTIVE INGREDIENTS: ALCOHOL; WATER

Tinnitus 4857L

INDICATIONS & USAGE SECTION

Formulated for associated symptoms such as ringing, buzzing, echoing, pressure, pain, throbbing and sensitivity to noise.

DOSAGE & ADMINISTRATION SECTION

Directions: Ages 12 and up, take 6 drops by mouth (ages 6 to 11, give 3 drops) as needed or as directed by a health professional.

OTC - ACTIVE INGREDIENT SECTION

Equal parts of Hydrastis canadensis 11x, Aconitum napellus 20x, Baryta carbonica 20x, Baryta muriatica 20x, Capsicum annuum 20x, Causticum 20x, Chenopodium anthelminticum 20x, Chininum sulphuricum 20x, Cinchona officinalis 20x, Glonoinum 20x, Graphites 20x, Hydrastis canadensis 20x, Kali bichromicum 20x, Kali muriaticum 20x, Lycopodium clavatum 20x, Phosphorus 20x, Pulsatilla 20x, Salicylicum acidum 20x, Tabacum 20x, Thiosinaminum 20x, Viola odorata 20x.

OTC - PURPOSE SECTION

Formulated for associated symptoms such as ringing, buzzing, echoing, pressure, pain, throbbing and sensitivity to noise.

INACTIVE INGREDIENT SECTION

Inactive Ingredients: USP Purified Water; USP Gluten-free, non-GMO, organic cane alcohol 20%

QUESTIONS SECTION

newtonlabs.net -Questions? 800.448.7256

Newton Laboratories, Inc. FDA Est # 1051203 - Conyers, GA 30013

WARNINGS SECTION

WARNINGS: Keep out of reach of children. Do not use if tamper-evident seal is broken or missing. If symptoms worsen or persist for more than a few days, consult a doctor. If pregnant or breast-feeding, ask a doctor before use.

OTC - PREGNANCY OR BREAST FEEDING SECTION

WARNINGS: If pregnant or breast-feeding, ask a doctor before use.

OTC - KEEP OUT OF REACH OF CHILDREN SECTION

WARNINGS: Keep out of reach of children.